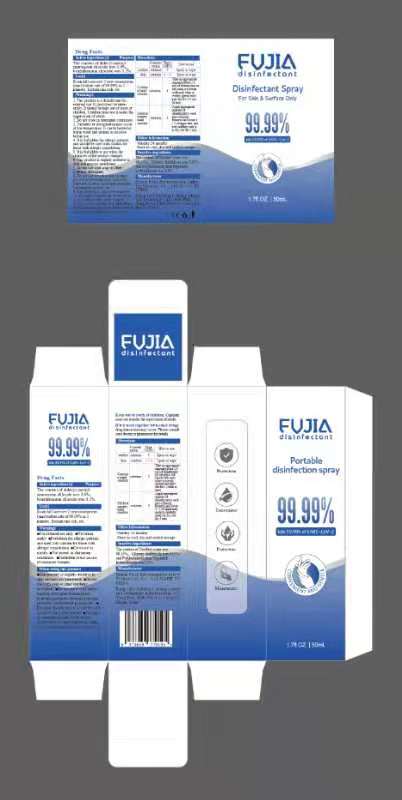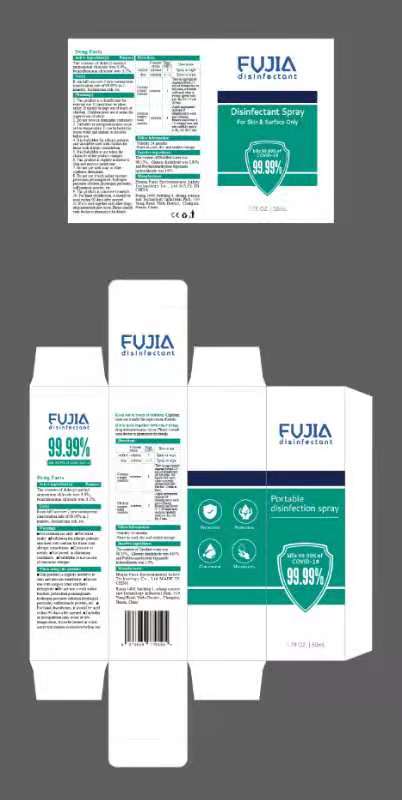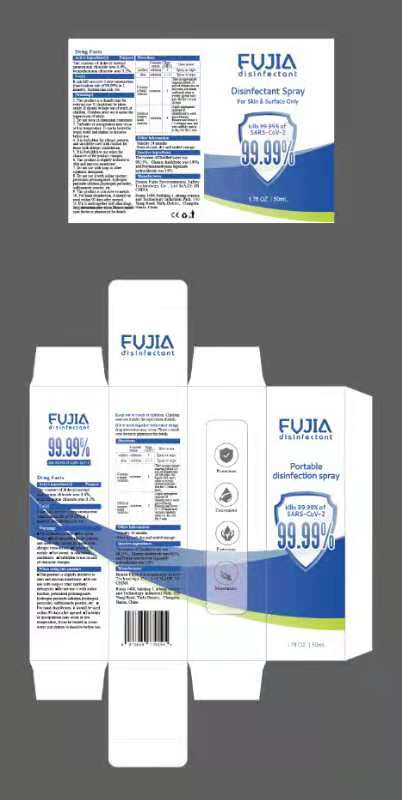 DRUG LABEL: FVJIA disinfectant
NDC: 82170-101 | Form: SPRAY
Manufacturer: Hunan Fujia Environmental Safety Technology Co., Ltd
Category: otc | Type: HUMAN OTC DRUG LABEL
Date: 20220518

ACTIVE INGREDIENTS: BENZALKONIUM CHLORIDE 0.2 g/100 mL; DIDECYLDIMONIUM CHLORIDE 0.6 g/100 mL
INACTIVE INGREDIENTS: POLIHEXANIDE HYDROCHLORIDE; GLUTARALDEHYDE; WATER

FVJIA disinfectant

Active Ingredient(s)

Didecyl Dimethyl Ammonium Chloride 0.60g/100mL

Benzalkonium chloride 0.20g/100mL

Purpose

Antiseptic

Use

FVJIA disinfectant to help reduce bacteria that potentially can cause disease. For use when soap and water are not available.

Warnings

For external use only.

Do not use

- in children less than 2 months of age
- on open skin wounds

When using this product keep out of eyes, ears, and mouth. In case of contact with eyes, rinse eyes thoroughly with water.
Stop use and ask a doctor if irritation or rash occurs. These may be signs of a serious condition.
Keep out of reach of children. If swallowed, get medical help or contact a Poison Control Center right away.

Stop use and ask a doctor if irritation or rash occurs. These may be signs of a serious condition.

Keep out of reach of children. If swallowed, get medical help or contact a Poison Control Center right away.

Directions

- Spray on the surface of the skin and let it dry naturally

Other information

- Store between 15-30C (59-86F)
- Avoid freezing and excessive heat above 40C (104F)

Inactive ingredients

Polyhexamethylene biguanide hydrochloride
Distilled water
Glutaric dialdehyde